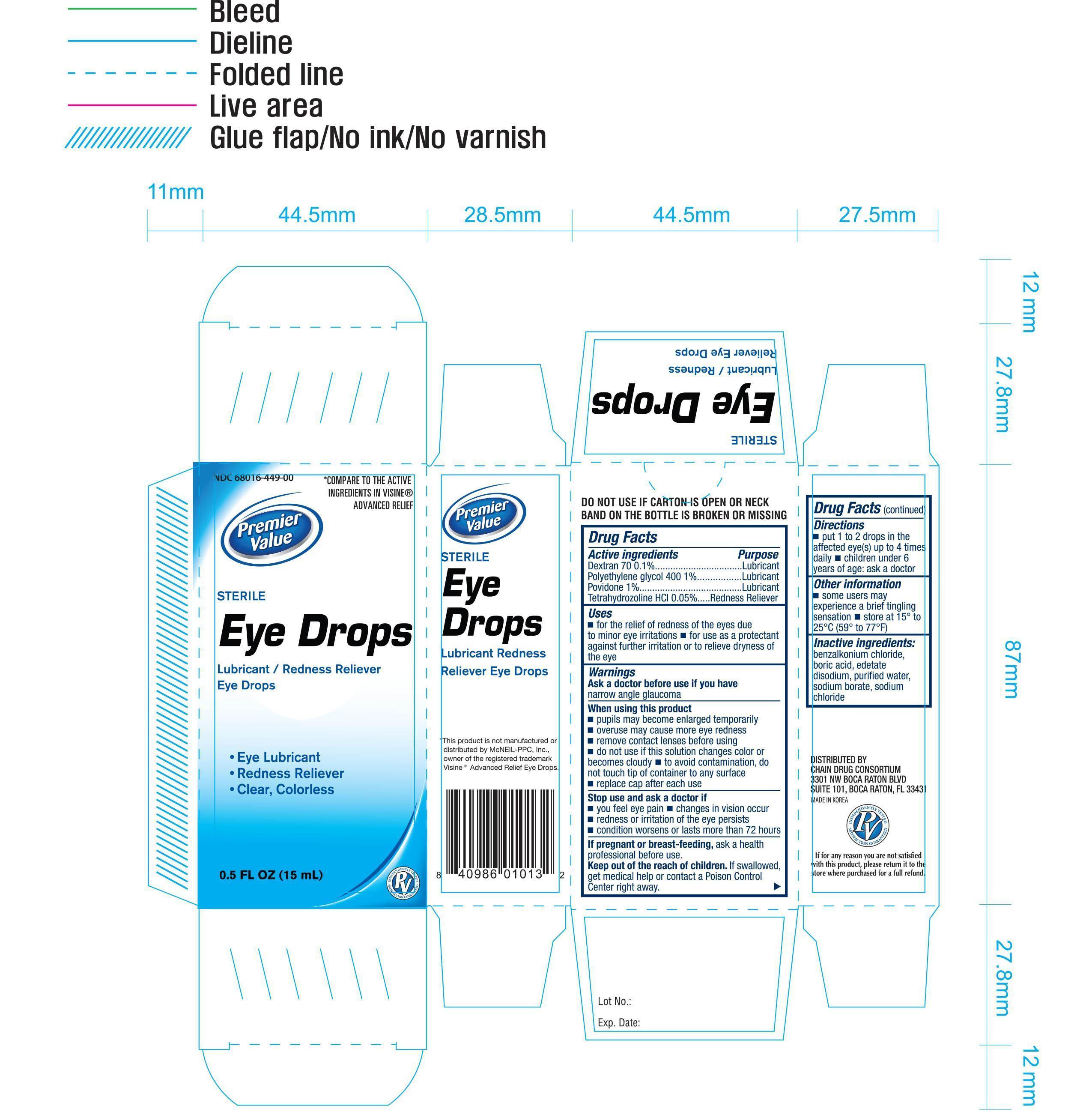 DRUG LABEL: Premier Value Sterile Eye Drops
NDC: 68016-449 | Form: SOLUTION/ DROPS
Manufacturer: Chain Drug Consortium, LLC
Category: otc | Type: HUMAN OTC DRUG LABEL
Date: 20140123

ACTIVE INGREDIENTS: DEXTRAN 70 .001 mg/1 mL; POLYETHYLENE GLYCOL 400 .01 mg/1 mL; POVIDONE .01 mg/1 mL; TETRAHYDROZOLINE HYDROCHLORIDE .0005 mg/1 mL
INACTIVE INGREDIENTS: BENZALKONIUM CHLORIDE; BORIC ACID; EDETATE DISODIUM; WATER; SODIUM BORATE; SODIUM CHLORATE

Active Ingredients Purpose

Dextran 70 0.1%........................................... Lubricant

Polyethylene glycol 400 1%............................. Lubricant

Povidone 1%................................................. Lubricant

Tetrahydrozoline HCI 0.05%............................ Redness Reliever

Uses

- for the relief of redness of the eyes due to minor eye irritations
- for use as a protectant against further irritation or to relieve dryness of the eye

Warnings

Ask a doctor before use if you have narrow angle glaucoma

When using this product

- pupils may become enlarged temporarily
- overuse may cause more eye redness
- remove contact lenses before using
- do not use if this solution changes color or becomes cloudy
- to avoid contamination, do not touch tip of container to any surface
- replace cap after each use

Stop use and ask a doctor if

- you feel eye pain
- changes in vision occur
- redness or irritation of the eye persists
- condition worsens or lasts for more than 72 hours

PREGNANCY OR BREAST FEEDING

If pregnant or breast-feeding, ask a health professional before use.

KEEP OUT OF REACH OF CHILDREN

Keep our of the reach of children. If swallowed, get medical help or contact a Poision Control Center right away.

Directions

- put 1 to 2 drops in the affected eye(s) up to 4 times daily
- children under 6 years of age: ask a doctor

Other information

- some users may experience a brief tingling sensation
- store at 15° to 25°C (59° to 77°F)

Inactive ingredients

benzalkonium chloride, boric acid, edetate disodium, purified water, sodium borate, sodium chloride

DOSAGE AND ADMINISTRATION

DISTRIBUTED BY:

CHAIN DRUG CONSORTIUM

3301 NW BOCA RATON BLVD

SUITE 101, BOCA RATON, FL 33431 USA